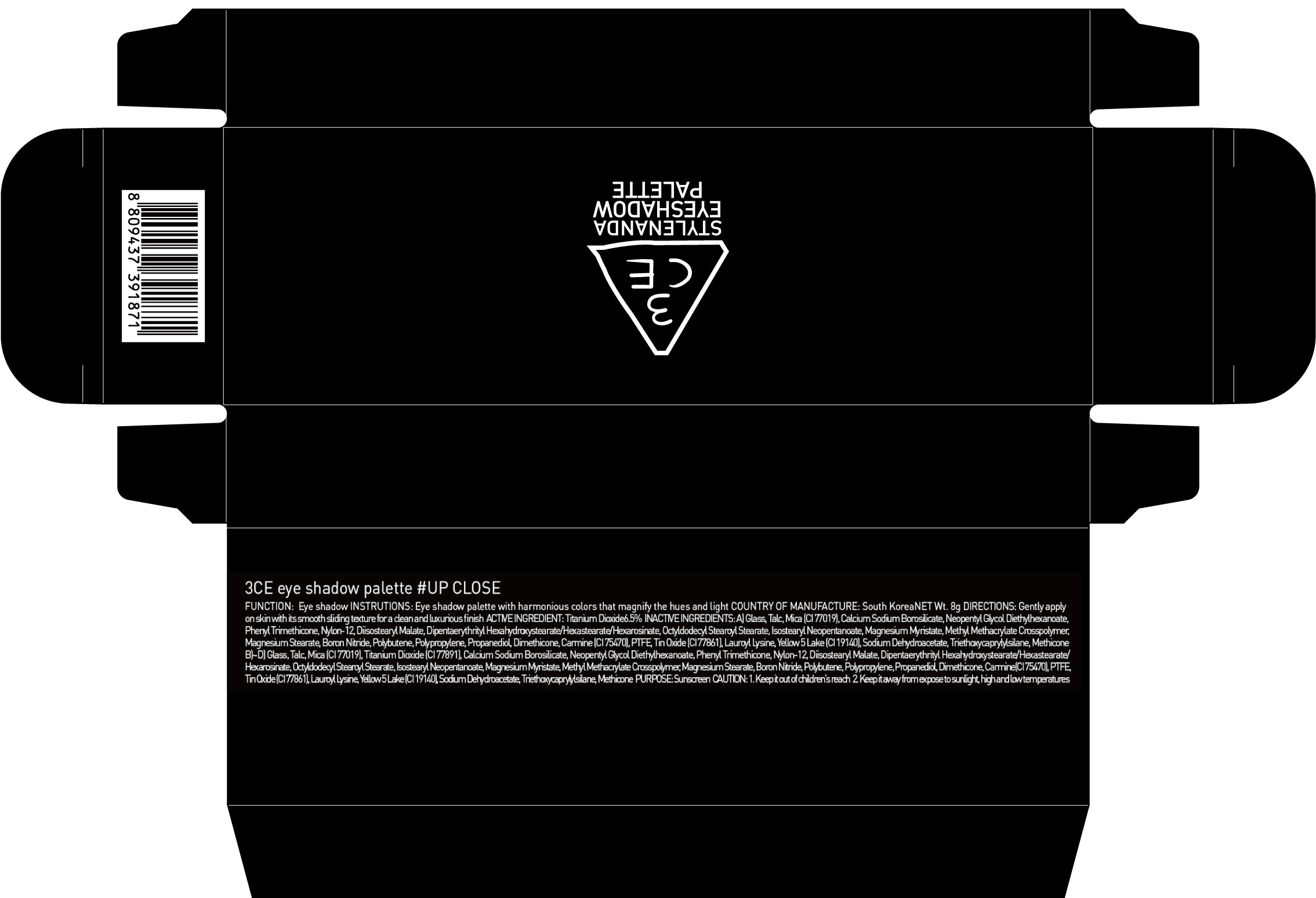 DRUG LABEL: 3CE EYE SHADOW PALETTE UP CLOSE
NDC: 60764-063 | Form: POWDER
Manufacturer: Nanda Co., Ltd
Category: otc | Type: HUMAN OTC DRUG LABEL
Date: 20161004

ACTIVE INGREDIENTS: Titanium Dioxide 0.52 g/8 g
INACTIVE INGREDIENTS: Talc; Mica

ACTIVE INGREDIENT

Active Ingredient: Titanium Dioxide 6.5%

INACTIVE INGREDIENT

Inactive Ingredients:

A) Glass, Talc, Mica (CI 77019), Calcium Sodium Borosilicate, Neopentyl Glycol Diethylhexanoate, Phenyl Trimethicone, Nylon-12, Diisostearyl Malate, Dipentaerythrityl Hexahydroxystearate/Hexastearate/Hexarosinate, Octyldodecyl Stearoyl Stearate, Isostearyl Neopentanoate, Magnesium Myristate, Methyl Methacrylate Crosspolymer, Magnesium Stearate, Boron Nitride, Polybutene, Polypropylene, Propanediol, Dimethicone, Carmine (CI 75470), PTFE, Tin Oxide (CI 77861), Lauroyl Lysine, Yellow 5 Lake (CI 19140), Sodium Dehydroacetate, Triethoxycaprylylsilane, Methicone

B)~D) Glass, Talc, Mica (CI 77019), Titanium Dioxide (CI 77891), Calcium Sodium Borosilicate, Neopentyl Glycol Diethylhexanoate, Phenyl Trimethicone, Nylon-12, Diisostearyl Malate, Dipentaerythrityl Hexahydroxystearate/Hexastearate/Hexarosinate, Octyldodecyl Stearoyl Stearate, Isostearyl Neopentanoate, Magnesium Myristate, Methyl Methacrylate Crosspolymer, Magnesium Stearate, Boron Nitride, Polybutene, Polypropylene, Propanediol, Dimethicone, Carmine (CI 75470), PTFE, Tin Oxide (CI 77861), Lauroyl Lysine, Yellow 5 Lake (CI 19140), Sodium Dehydroacetate, Triethoxycaprylylsilane, Methicone

PURPOSE

Purpose: Sunscreen

CAUTION

CAUTION: 1. Keep it out of children's reach 2. Keep it away from expose to sunlight, high and low temperatures.

DESCRIPTION

INSTRUCTIONS: Eye shadow palette with harmonious colors that magnify the hues and light.

Directions: Gently apply on skin with its smooth sliding texture for a clean and luxurious finish